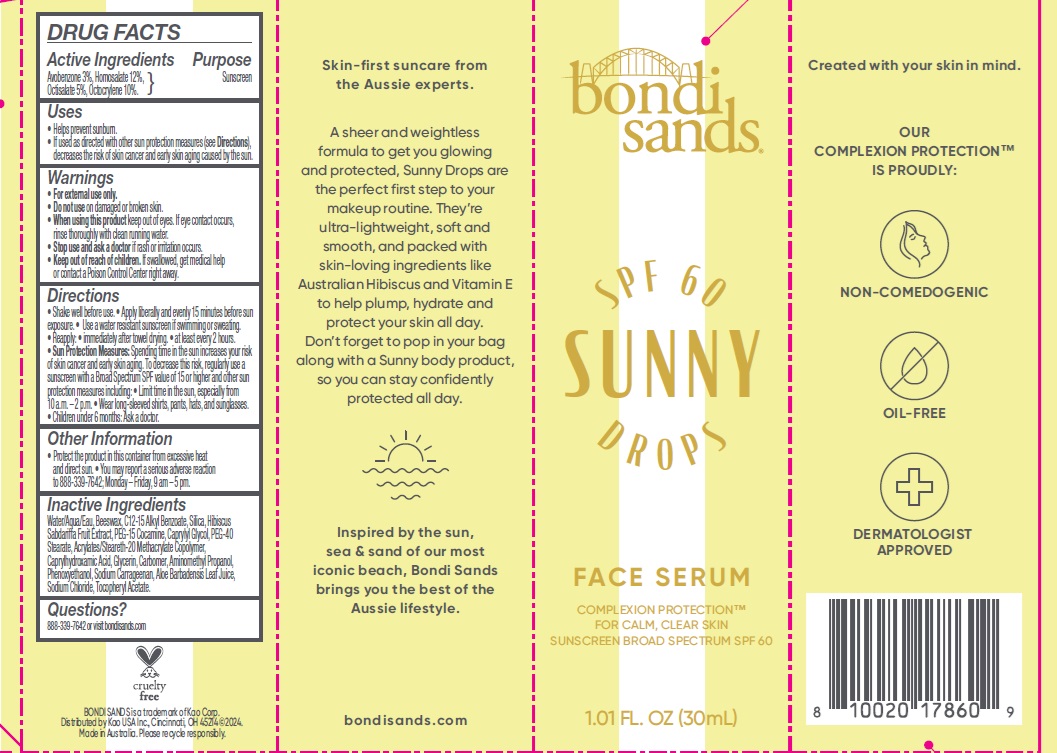 DRUG LABEL: Bondi Sands SPF 60 Sunny Drops Face Serum
NDC: 79950-021 | Form: LOTION
Manufacturer: BONDI SANDS (USA) INC.
Category: otc | Type: HUMAN OTC DRUG LABEL
Date: 20250110

ACTIVE INGREDIENTS: AVOBENZONE 30 mg/1 mL; OCTISALATE 50 mg/1 mL; OCTOCRYLENE 100 mg/1 mL; HOMOSALATE 120 mg/1 mL
INACTIVE INGREDIENTS: CAPRYLYL GLYCOL; AMINOMETHYL PROPANOL; WATER; BEESWAX; PEG-40 STEARATE; .ALPHA.-TOCOPHEROL ACETATE; ACRYLATES/STEARETH-20 METHACRYLATE COPOLYMER; SODIUM CHLORIDE; CAPRYLHYDROXAMIC ACID; PHENOXYETHANOL; GLYCERIN; CARBOMER; SODIUM CARRAGEENAN; ALOE VERA LEAF; PEG-15 COCAMINE; SILICON DIOXIDE; C12-15 ALKYL BENZOATE

Bondi Sands SPF 60 Sunny Drops Face Serum

Active Ingredients

Avobenzone 3%

Homosalate 12%

Octisalate 5%

Octocrylene 10%

Purpose

Sunscreen

Uses

- Helps prevent sunburn.
- If used as directed with other sun protection measures (see Directions), decreases the risk of skin cancer and early skin aging caused by the sun.

Warnings

- For external use only

Do not use

on damaged or broken skin.

When using this product

keep out of eyes. If eye contact occurs, rinse thoroughly with clean running water.

Stop use and ask a doctor

if rash or irritation occurs.

Keep out of reach of children.

If swallowed, get medical help or contact a Poison Control Center right away.

Directions

- Shake well before use.
- Apply liberally and evenly 15 minutes before sun exposure.
- Use a water resistant sunscreen if swimming or sweating.
- Reapply:
- immediately after towel drying.
- at least every 2 hours.
- Sun Protection Measures: Spending time in the sun increases your risk of skin cancer and early skin aging. To decrease this risk, regularly use a sunscreen with a Broad Spectrum SPF value of 15 or higher and other sun protection measures including:
- Limit time in the sun, especially from 10 a.m. – 2 p.m.
- Wear long-sleeved shirts, pants, hats, and sunglasses.
- Children under 6 months: Ask a doctor.

Other Information

- Protect the product in this container from excessive heat and direct sun.
- You may report a serious adverse reaction to 888-339-7642; Monday – Friday, 9 am – 5 pm.

Inactive Ingredients

Water/Aqua/Eau, Beeswax, C12-15 Alkyl Benzoate, Silica, Hibiscus Sabdariffa Fruit Extract, PEG-15 Cocamine, Caprylyl Glycol, PEG-40 Stearate, Acrylates/Steareth-20 Methacrylate Copolymer, Caprylhydroxamic Acid, Glycerin, Carbomer, Aminomethyl Propanol, Phenoxyethanol, Sodium Carrageenan, Aloe Barbadensis Leaf Juice, Sodium Chloride, Tocopheryl Acetate.

Questions?

888-339-7642 or visit bondisands.com